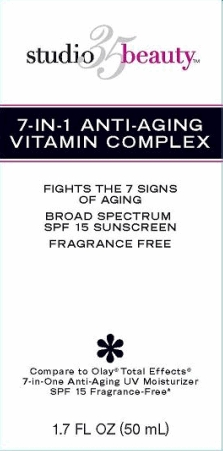 DRUG LABEL: Walgreens 7-in-1 Anti-Aging Vitamin Complex Broad Spectrum SPF 15 Sunscreen
NDC: 0363-0692 | Form: CREAM
Manufacturer: Walgreen Company
Category: otc | Type: HUMAN OTC DRUG LABEL
Date: 20140110

ACTIVE INGREDIENTS: AVOBENZONE 3 mg/100 mL; OCTISALATE 5 mg/100 mL; OCTOCRYLENE 8 mg/100 mL
INACTIVE INGREDIENTS: WATER; ISOPROPYL ISOSTEARATE; BORON NITRIDE; CARBOXYMETHYLCELLULOSE SODIUM; POLYACRYLAMIDE (10000 MW); C13-14 ISOPARAFFIN; LAURETH-7; CETYL ALCOHOL; STEARYL ALCOHOL; CYCLOMETHICONE; DIMETHICONOL (100000 CST); DIMETHICONE; CETOSTEARYL ALCOHOL; CETEARYL GLUCOSIDE; PHENOXYETHANOL; METHYLPARABEN; ETHYLPARABEN; BUTYLPARABEN; PROPYLPARABEN; ISOBUTYLPARABEN; SORBITAN MONOSTEARATE; PANTHENOL; DOCOSANOL; .ALPHA.-TOCOPHEROL ACETATE; BENZYL ALCOHOL; EDETATE DISODIUM; PEG-100 STEARATE; STEARIC ACID; ASCORBYL TETRAISOPALMITATE; MAGNESIUM ASPARTATE; ZINC GLUCONATE; COPPER GLUCONATE; CALCIUM GLUCONATE; DIHYDROXYACETONE

studio 35 beauty™ 7-IN-1 ANTI-AGING VITAMIN COMPLEX

Active ingredient

Avobenzone 3.0%
Octisalate 5.0%
Octocrylene 8.0%

Purpose

Sunscreen

Uses

- helps prevent sunburn
- If used as directed with other sun protection measures (see Directions), decreases the risk of skin cancer and early skin aging caused by the sun

Warnings

For external use only.

Do not use on

- damaged or broken skin.

When using this product

- keep out of eyes. Rinse with water to remove.

Stop use and ask a doctor

- if rash occurs.

Keep Out of Reach of Children.

If swallowed, get medical help or contact a Poison Control Center right away.

Directions

- Apply liberally 15 minutes before sun exposure.
- Children under 6 months of age: ask a doctor
- Sun Protection Measures: Spending time in the sun increases your risk of skin cancer and early skin aging. To decrease this risk, regularly use a sunscreen with a Broad Spectrum SPF value of 15 or higher and other sun protection measures including:
  - limit time in the sun, especially from 10 a.m. - 2 p.m.
  - wear long-sleeved shirts, pants, hats and sunglasses

Other Information

- protect the product in this container from excessive heat and direct sun

Inactive ingredients

water, glycerin, isopropyl isostearate, boron nitride, sodium carboxymethyl beta-glucan, polyacrylamide, C13-14 isoparaffin, laureth-7, cetyl alcohol, stearyl alcohol, cyclopentasiolxane, dimethiconol, dimethicone, cetearyl alcohol, cetearyl glucoside, phenoxyethanol, methylparaben, ethylparaben, butylparaben, propylparaben, isobutylparaben, sorbitan stearate, panthenol (pro-vitamin B5), behenyl alcohol, tocopheryl acetate (vitamin E), benzyl alcohol, disodium EDTA, PEG-100 stearate, stearic acid, ascorbyl tetraisopalmitate, magnesium aspartate, zinc gluconate, copper gluconate, calcium gluconate, dihydroxyacetone

Package/Label Principal Display Panel

studio 35 beauty™ 7-IN-1 ANTI-AGING VITAMIN COMPLEX

Fights the 7 Signs of Aging
Broad Spectrum SPF30 Sunscreen
Fragrance Free

Compare to Olay® Total Effects®
7-in-One Anti-Aging UV Moisturizer
SPF 15 Fragrance-Free*

1.7 Fl Oz (50 mL)

Distributed by: Walgreen Co.
200 Wilmot Rd., Deerfield, IL 60015
100% Satisfaction Guaranteed

walgreens.com ©2012 Walgreen Co.

Made in Israel

Carton Label